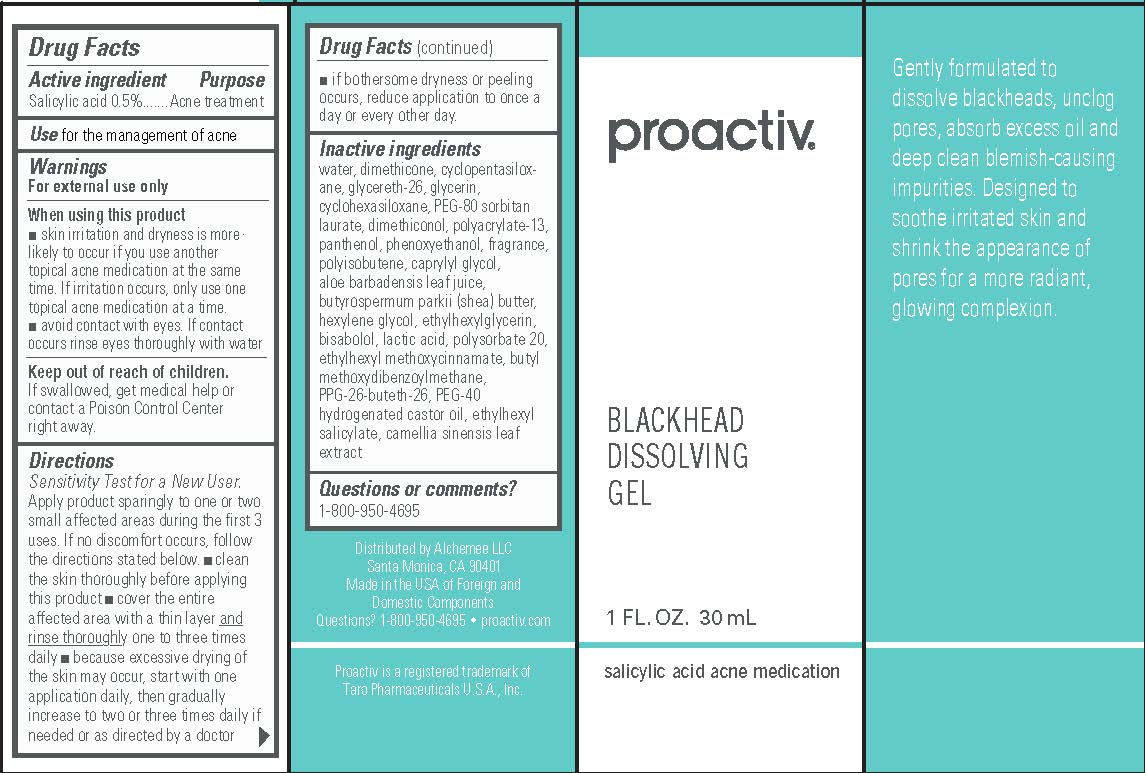 DRUG LABEL: Proactiv Blackhead Dissolving
NDC: 11410-024 | Form: GEL
Manufacturer: Alchemee, LLC
Category: otc | Type: HUMAN OTC DRUG LABEL
Date: 20260107

ACTIVE INGREDIENTS: SALICYLIC ACID 0.5 g/100 mL
INACTIVE INGREDIENTS: WATER; DIMETHICONE; CYCLOMETHICONE 5; GLYCERETH-26; GLYCERIN; CYCLOMETHICONE 6; DIMETHICONOL (40 CST); PANTHENOL; GREEN TEA LEAF; ALOE VERA LEAF; SHEA BUTTER; LEVOMENOL; LACTIC ACID, UNSPECIFIED FORM; CAPRYLYL GLYCOL; ETHYLHEXYLGLYCERIN; POLYOXYL 40 HYDROGENATED CASTOR OIL; POLYISOBUTYLENE (1300 MW); HEXYLENE GLYCOL; POLYSORBATE 20; PPG-26-BUTETH-26; AVOBENZONE; OCTINOXATE; OCTISALATE; PHENOXYETHANOL; POLYACRYLAMIDE (1300000 MW); PEG-80 SORBITAN LAURATE

Proactiv®Blackhead Dissolving Gel

Drug Facts

Active ingredient

Salicylic acid 0.5%

Purpose

Acne treatment

Use

for the management of acne

Warnings

For external use only

When using this product

- skin irritation and dryness is more likely to occur if you use another topical acne medication at the same time. If irritation occurs, only use one topical acne medication at a time.
- avoid contact with eyes. If contact occurs, rinse eyes thoroughly with water.

Keep out of reach of children.

If swallowed, get medical help or contact a Poison Control Center right away.

Directions

- Sensitivity Test for a New User. Apply product sparingly to one or two small affected areas during the first 3 uses. If no discomfort occurs, follow the directions stated below.
- clean the skin thoroughly before applying this product
- cover the entire affected area with a thin layer and rinse thoroughly one to three times daily
- because excessive drying of the skin may occur, start with one application daily, then gradually increase to two or three times daily if needed or as directed by a doctor
- if bothersome dryness or peeling occurs, reduce application to once a day or every other day.

Inactive ingredients

water, dimethicone, cyclopentasiloxane, glycereth-26, glycerin, cyclohexasiloxane, PEG-80 sorbitan laurate, dimethiconol, polyacrylate-13, panthenol, phenoxyethanol, fragrance, polyisobutene, caprylyl glycol, aloe barbadensis leaf juice, butyrospermum parkii (shea) butter, hexylene glycol, ethylhexylglycerin, bisabolol, lactic acid, polysorbate 20, ethylhexyl methoxycinnamate, butyl methoxydibenzoylmethane, PPG-26-buteth-26, PEG-40 hydrogenated castor oil, ethylhexyl salicylate, camellia sinensis leaf extract

Questions or comments?

1-800-950-4695

Distributed by Alchemee LLC
Santa Monica, CA 90401
Made in the USA of Foreign and
Domestic Components
Questions? 1-800-950-4695 • proactiv.com
Proactiv is a registered trademark of
Taro Pharmaceuticals U.S.A., Inc.

PRINCIPAL DISPLAY PANEL - 30 mL Tube Box

proactiv®

BLACKHEAD
DISSOLVING
GEL

1 FL. OZ. 30 mL

salicylic acid acne medication